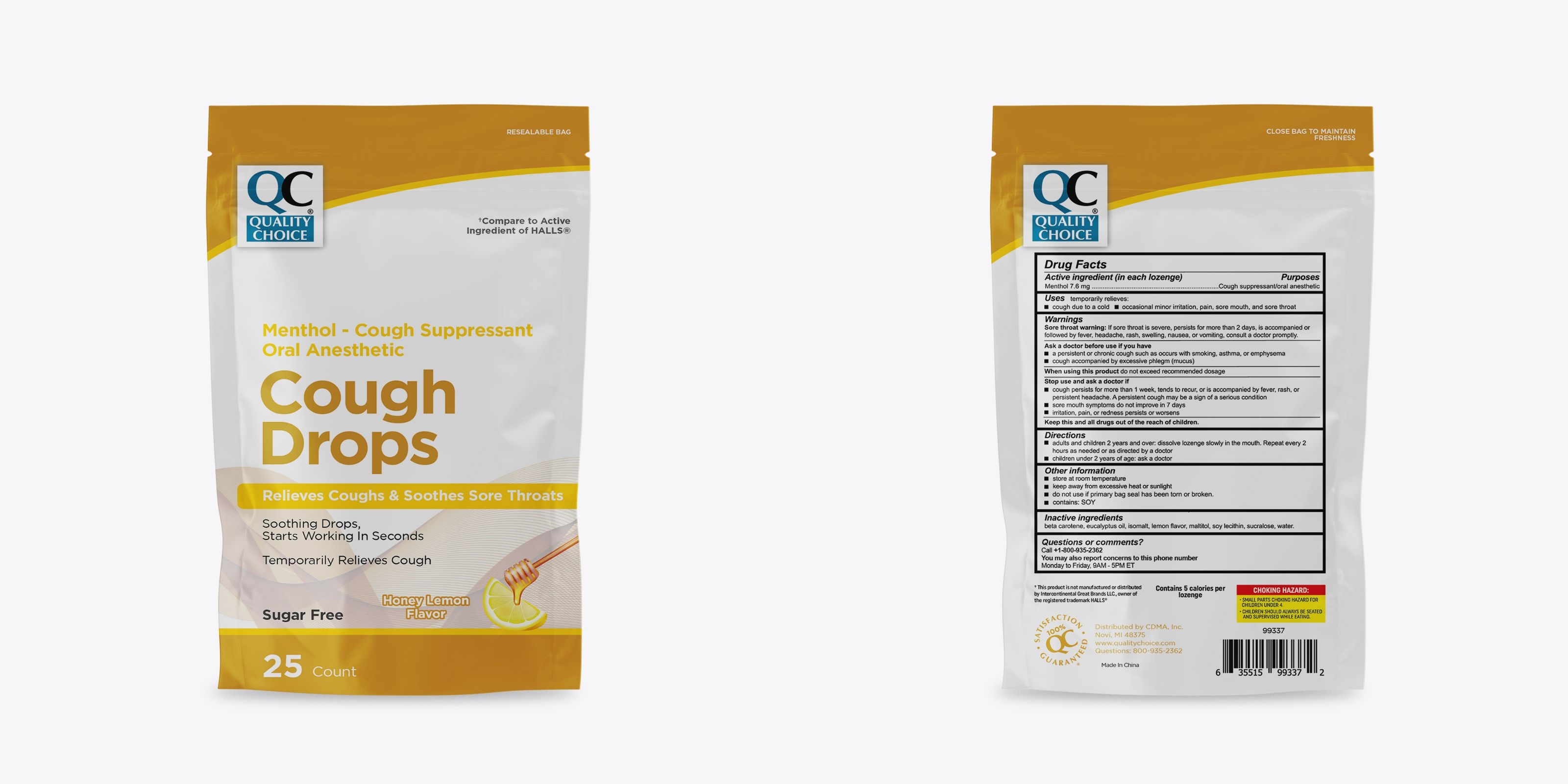 DRUG LABEL: Quality Choice Honey Lemon Sugar Free Cough Drops
NDC: 83324-288 | Form: LOZENGE
Manufacturer: Chain Drug Marketing Association, Inc.
Category: otc | Type: HUMAN OTC DRUG LABEL
Date: 20251222

ACTIVE INGREDIENTS: MENTHOL 7.6 mg/1 1
INACTIVE INGREDIENTS: BETA CAROTENE; ISOMALT; MALTITOL; EUCALYPTUS OIL; SUCRALOSE; LECITHIN, SOYBEAN; WATER

Quality Choice Honey Lemon Sugar Free Cough Drops

Warnings

Sore throat warning: If sore throat is severe, persists for more than 2 days, is accompanied or followed by fever, headache, rash, swelling, nausea, or vomiting, consult a doctor promptly.

Purpose

Purposes cough suppressant, oral anesthetic

Active Ingredient(s)

Menthol 7.6 mg

Use

temporary relieves: ■ cough due to cold ■ occasional minor irritation, pain, sore mouth, and sore throat

Ask a doctor before use if you have: ■ persistent or chronic cough such as occurs with smoking, asthma, or emphysema ■ cough accompanied by excessive phlegm (mucus).

Stop use and ask a doctor if ■ cough persists for more than 1 week, tends to recur, or is accompained by fever, rash, or persistent headache. A persistant cough may be a sign of a serius condition. ■ sore mouth symptoms do not improve in 7 days ■ irritation, pain, or redness persists or worsens.

KEEP OUT OF REACH OF CHILDREN

Keep this and all drugs out of reach of children.

Directions

■ adults and children 5 years and over: dissolve lozenge slowly in the mouth. Repeat every 2 hours as needed or as directed by a doctor

■ children under 2 years of age: ask a doctor

Other information

■ store at room temperature

■ keep away from excessive heat or sunlight

■ do not use if primary bag seal has been torn or broken

■ contains: SOY

Inactive ingredients

Beta carotene, eucalyptus oil, isomalt, lemon flavor, maltitol, soy lecithin, sucralose, water

QUESTIONS

Call +1800-935-2362

You may also report concerns to this phone number

Monday to Friday, 9AM - 5PM ET

RECENT MAJOR CHANGES

[Indications and Usage Section]: Minor editing was done to comply with monograph wording of uses. Changes were made Nov 2024.

[Dosage and Administration Section]: Minor editing was done to improve section clarity. No changes were made to dosage or administration. Changes were made Nov 2024.

Package Label - Principal Display Panel

25 Drops NDC: 83324-288-25